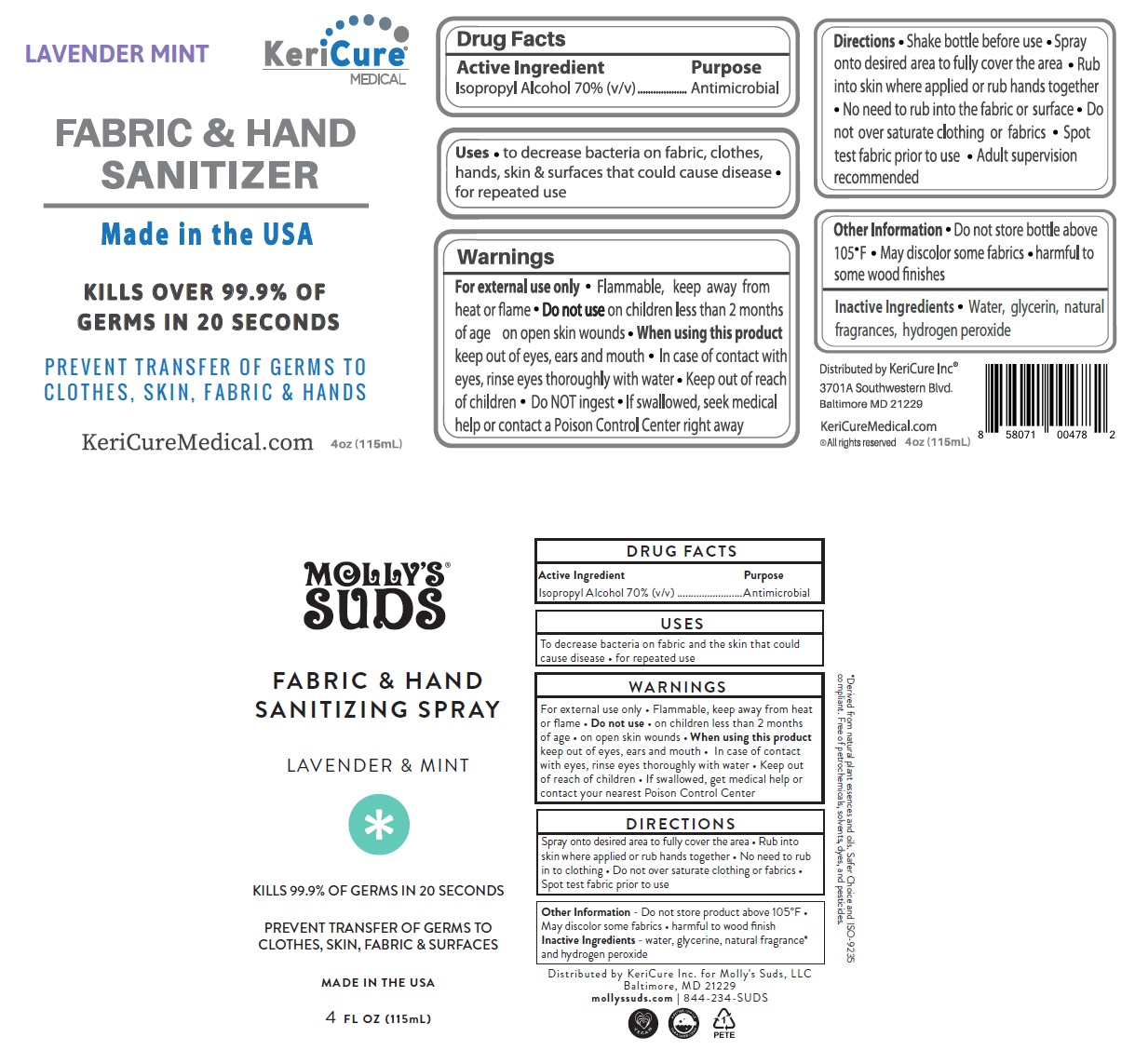 DRUG LABEL: KeriCure Fabric and Hand Sanitizer
NDC: 78280-314 | Form: SPRAY
Manufacturer: Kericure Inc.
Category: otc | Type: HUMAN OTC DRUG LABEL
Date: 20200715

ACTIVE INGREDIENTS: ISOPROPYL ALCOHOL 70 mL/100 mL
INACTIVE INGREDIENTS: WATER; GLYCERIN; HYDROGEN PEROXIDE

KeriCure® MEDICAL FABRIC & HAND SANITIZER

Active Ingredient

Isopropyl Alcohol 70% (v/v)

Purpose

Antimicrobial

INDICATIONS AND USAGE

Uses • to decrease bacteria on fabric, clothes, hands, skin & surfaces that could cause disease • for repeated use

Warnings

For external use only • Flammable, keep away from heat or flame • Do not use on children less than 2 months of age on open skin wounds • When using this product keep out of eyes, ears and mouth • In case of contact with eyes, rinse eyes thoroughly with water • do NOT ingest • If swallowed, seek medical help or contact a Poison Control Center right away

• Keep out of reach of children

DOSAGE AND ADMINISTRATION

Directions • Shake bottle before use • Spray onto desired area to fully cover the area • Rub into skin where applied or rub hands together • No need to rub into the fabric or surface • Do not over saturate clothing or fabrics • Spot test fabrics prior to use • Adult supervision recommended

Other Information • Do not store bottle above 105°F • May discolor some fabrics • harmful to some wood finishes

INACTIVE INGREDIENT

Inactive Ingredients • Water, glycerin, natural fragrances, hydrogen peroxide

LAVENDER MINT

Made in the USA

KILLS OVER 99.9% OF GERMS IN 20 SECONDS

PREVENT TRANSFER OF GERMS TO CLOTHES, SKIN, FABRIC & HANDS

*Derived from natural plant essences and oils. Safer Choice and ISO-9235 compliant. Free of petrochemicals, solvents, dyes, and pesticides.

Distributed by KeriCure Inc®

3701A Southwestern Blvd.

Baltimore MD 21229

KeriCureMedical.com

®All rights reserved

Distributed by KeriCure Inc. for Molly's Suds, LLC

Baltimore, MD 21229

mollyssuds.com | 844-234-SUDS